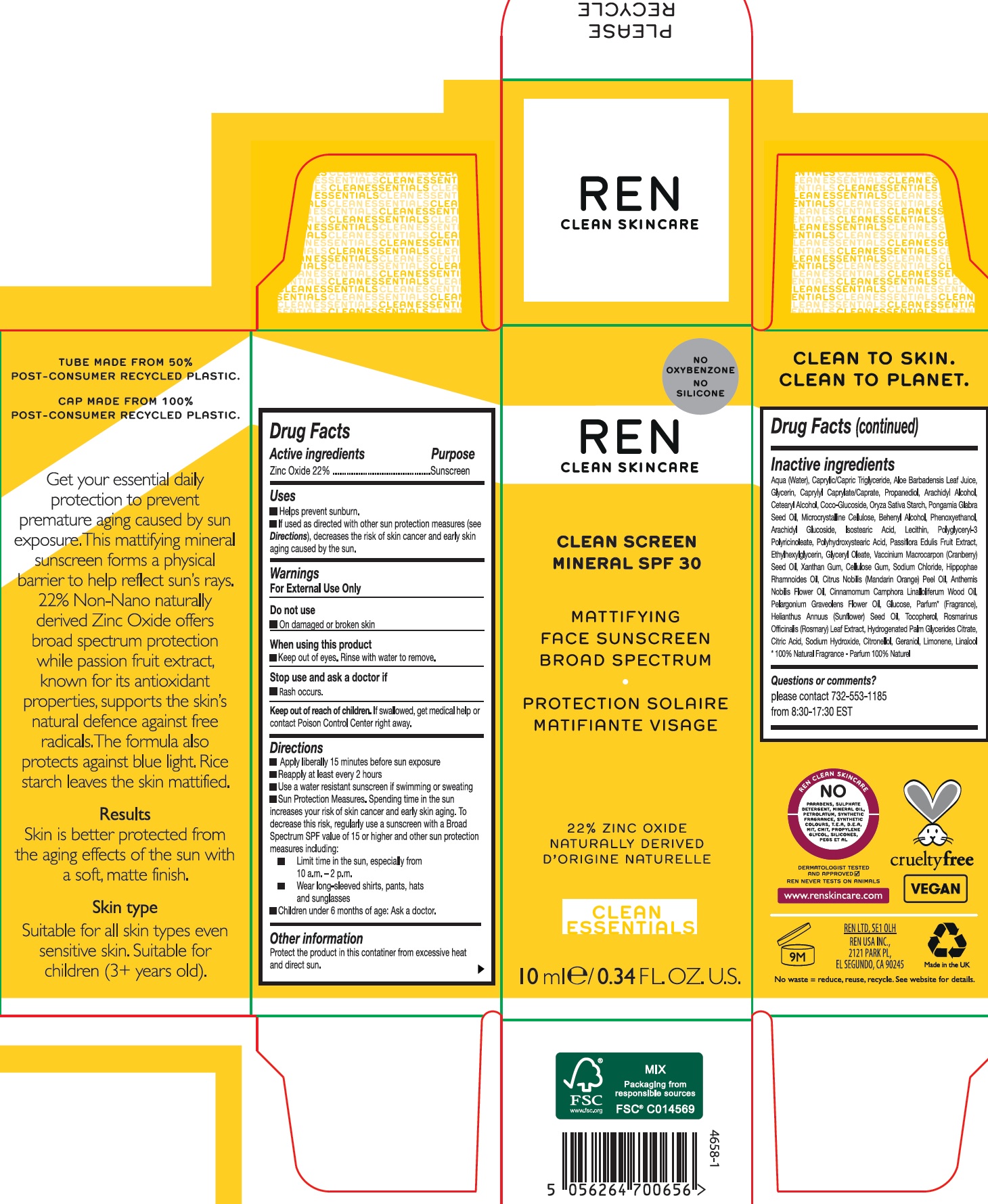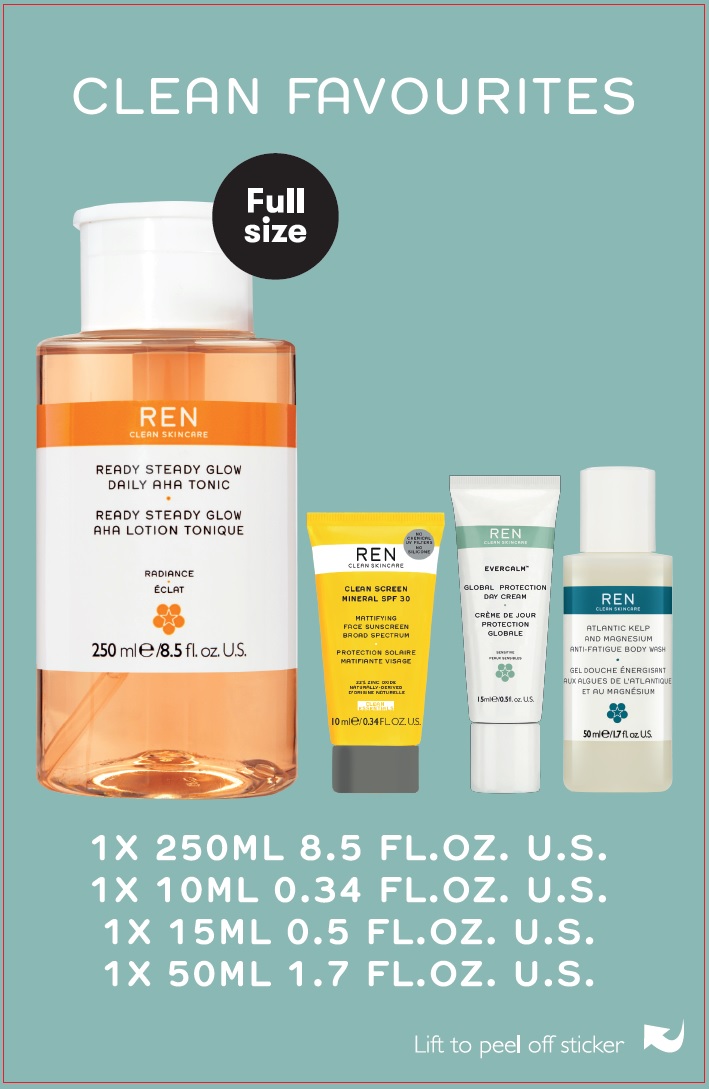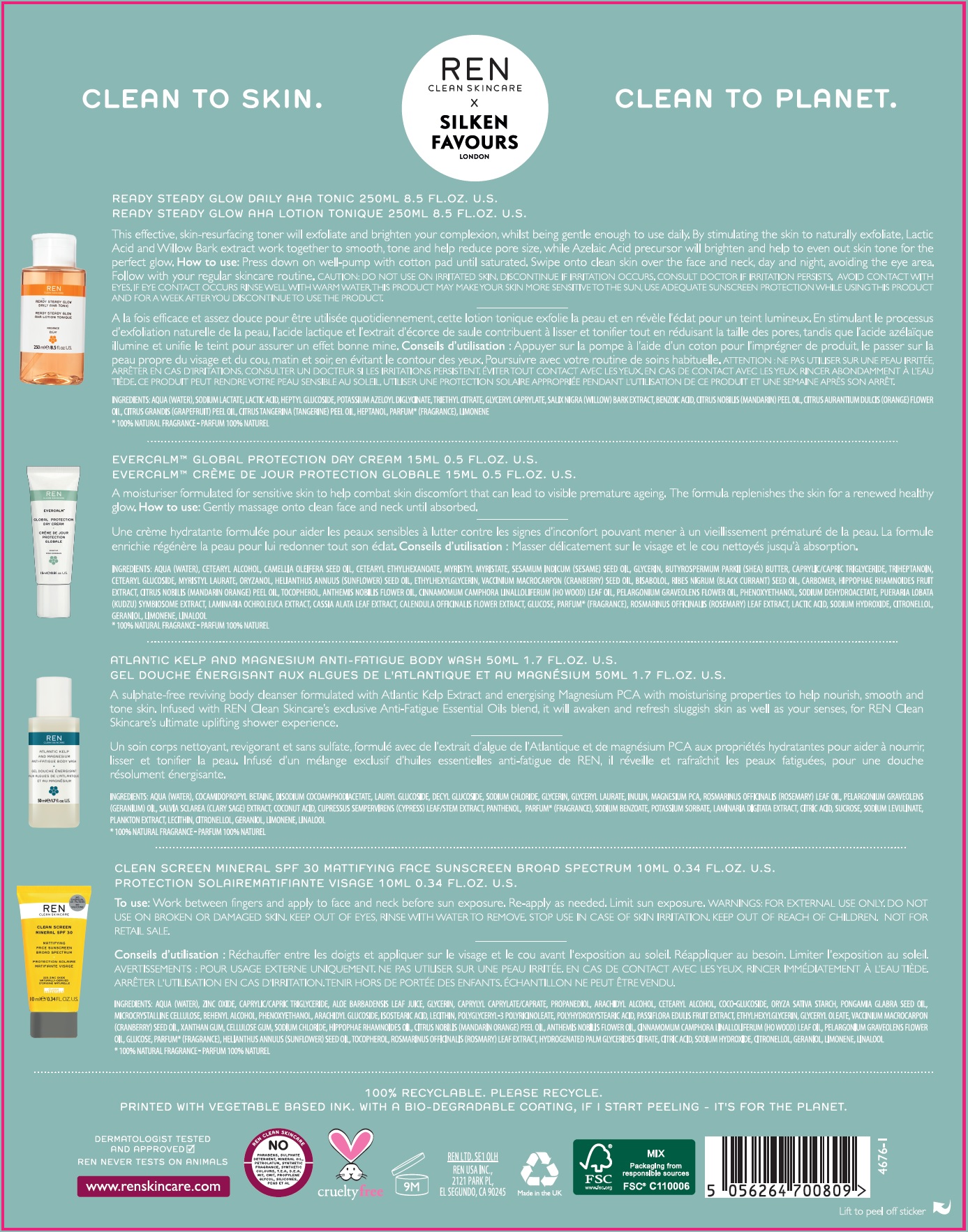 DRUG LABEL: REN Clean Favourites
NDC: 51417-0003 | Form: KIT | Route: TOPICAL
Manufacturer: REN Ltd
Category: otc | Type: HUMAN OTC DRUG LABEL
Date: 20231130

ACTIVE INGREDIENTS: ZINC OXIDE 220 mg/1 mL
INACTIVE INGREDIENTS: WATER; MEDIUM-CHAIN TRIGLYCERIDES; ALOE VERA LEAF; GLYCERIN; CAPRYLYL CAPRYLATE/CAPRATE; PROPANEDIOL; ARACHIDYL ALCOHOL; CETOSTEARYL ALCOHOL; COCO GLUCOSIDE; STARCH, RICE; KARUM SEED OIL; MICROCRYSTALLINE CELLULOSE; DOCOSANOL; PHENOXYETHANOL; ARACHIDYL GLUCOSIDE; ISOSTEARIC ACID; ETHYLHEXYLGLYCERIN; GLYCERYL OLEATE; CRANBERRY SEED OIL; XANTHAN GUM; CARBOXYMETHYLCELLULOSE SODIUM, UNSPECIFIED FORM; SODIUM CHLORIDE; MANDARIN OIL; CHAMAEMELUM NOBILE FLOWER OIL; PELARGONIUM GRAVEOLENS FLOWER OIL; ANHYDROUS DEXTROSE; SUNFLOWER OIL; TOCOPHEROL; CITRIC ACID MONOHYDRATE; SODIUM HYDROXIDE; LINALOOL, (+/-)-

REN Clean Favourites Kit

Active ingredients

Zinc Oxide 22%

Purpose

Sunscreen

Uses

- Helps prevent sunburn.
- If used as directed with other sun protection measures (see), decreases the risk of skin cancer and early skin aging caused by the sun. Directions

Warnings

For External Use Only

Do not use

- On damaged or broken skin

When using this product

- Keep out of eyes. Rinse with water to remove.

Stop use and ask a doctor if

- Rash occurs.

Keep out of reach of children.

If swallowed, get medical help or contact Poison Control Center right away.

Directions

- Apply liberally 15 minutes before sun exposure
- Reapply at least every 2 hours
- Use a water resistant sunscreen if swimming or sweating
- Sun Protection Measures. Spending time in the sun increases your risk of skin cancer and early skin aging. To decrease this risk, regularly use a sunscreen with a Broad Spectrum SPF value of 15 or higher and other sun protection measures including:
- Limit time in the sun, especially from 10 a.m. - 2p.m.
- Wear long-sleeved shirts, pants, hats and sunglasses
- Children under 6 months of age: Ask a doctor.

Other information

Protect the product in this container from excessive heat and direct sun.

Inactive ingredients

Aqua (Water), Caprylic/Capric Triglyceride, Aloe Barbadensis Leaf Juice, Glycerin, Caprylyl Caprylate/Caprate, Propanediol, Arachidyl Alcohol, Cetearyl Alcohol, Coco-Glucoside, Oryza Sativa Starch, Pongamia Glabra Seed Oil, Microcrystalline Cellulose, Behenyl Alcohol, Phenoxyethanol, Arachidyl Glucoside, Isostearic Acid, Lecithin, Polyglyceryl-3 Polyricinoleate, Polyhydroxystearic Acid, Passiflora Edulis Fruit Extract, Ethylhexylglycerin, Glyceryl Oleate, Vaccinium Macrocarpon (Cranberry) Seed Oil, Xanthan Gum, Cellulose Gum, Sodium Chloride, HippophaeRhamnoides Oil, Citrus Nobilis (Mandarin Orange) Peel Oil, Anthemis Nobilis Flower Oil, Cinnamomum Camphora Linalloliferum Wood Oil, Pelargonium Graveolens Flower Oil, Glucose, Parfum* (Fragrance), Helianthus Annuus (Sunflower) Seed Oil, Tocopherol, Rosmarinus Officinalis (Rosmary) Leaf Extract, Hydrogenated Palm Glycerides Citrate, Citric Acid, Sodium Hydroxide, Citronellol, Geraniol, Limonene, Linalool

*100% Natural Fragrance - Parfum 100% Naturel

Questions or comments?

please contact 800-437-3488 from 8:30-17:30 EST